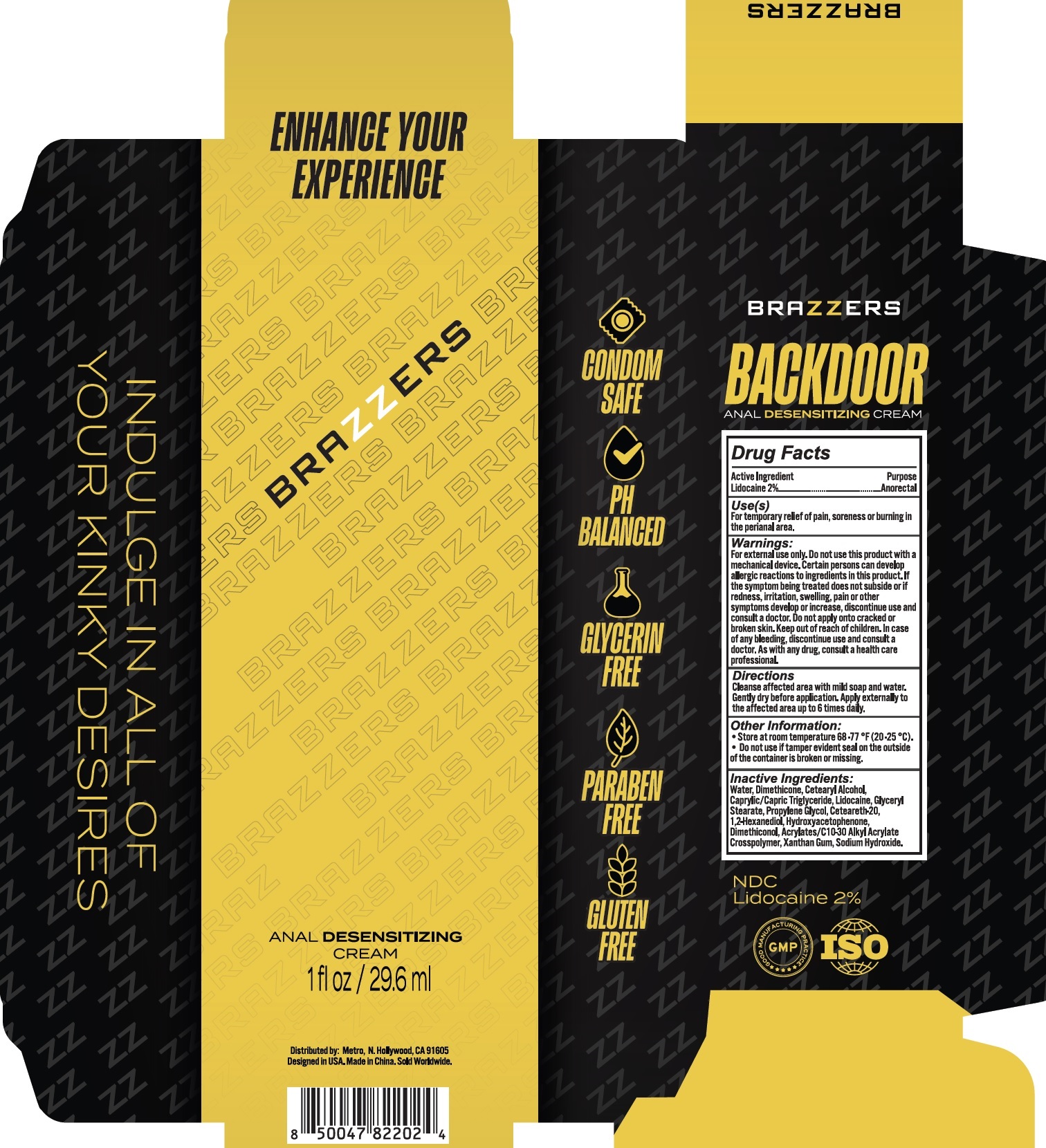 DRUG LABEL: Brazzers Anal Desensitizing
NDC: 83553-001 | Form: CREAM
Manufacturer: Metro Media Ent
Category: otc | Type: HUMAN OTC DRUG LABEL
Date: 20231106

ACTIVE INGREDIENTS: LIDOCAINE 20 mg/1 mL
INACTIVE INGREDIENTS: DIMETHICONE; CETOSTEARYL ALCOHOL; MEDIUM-CHAIN TRIGLYCERIDES; GLYCERYL MONOSTEARATE; WATER; PROPYLENE GLYCOL; POLYOXYL 20 CETOSTEARYL ETHER; 1,2-HEXANEDIOL; HYDROXYACETOPHENONE; XANTHAN GUM; SODIUM HYDROXIDE

Brazzers Anal Desensitizing Cream

Active Ingredient

Lidocaine 2%

Purpose

Anorectal

Use (s)

For temporary relief of pain, soreness or burning in the peritanal area.

Warnings:

For external use only.

Do not use

this product with a mechanical device. Certain persons can develop allergic reactions to ingredients in this product. If the symptom being treated does not subside or if redness, irritation, swelling, pain or other symptoms develop or increase, discontinue use and consult a doctor. Do not apply onto cracked or broken skin.

Keep out of reach of children.

In case of any bleeding, discontinue use and consult a doctor. As with any drug, consult a health care professional.

Directions

Cleanse affected area with mild soap and water. Gently dry before application. Apply externally to the affected area up to 6 times daily.

Other Information:

- Store at room temperture 68-77 °F (20-25 °C).
- Do not use if temper evident seal on the outside of the container is broken or missing.

Inactive Ingredients:

Water, Dimethicone, Cetearyl Alcohol, Caprylic/Capric Triglyceride, Lidocaine, Glyceryl Stearate, Propylene Glycol, Ceteareth-20, 1,2-Hexanediol, Hydroxyacetophenone, Dimethiconal, Acrylates/C10-30 Alkyl Acrylate Crosspolymer, Xanthan Gum, Sodium Hydroxide.